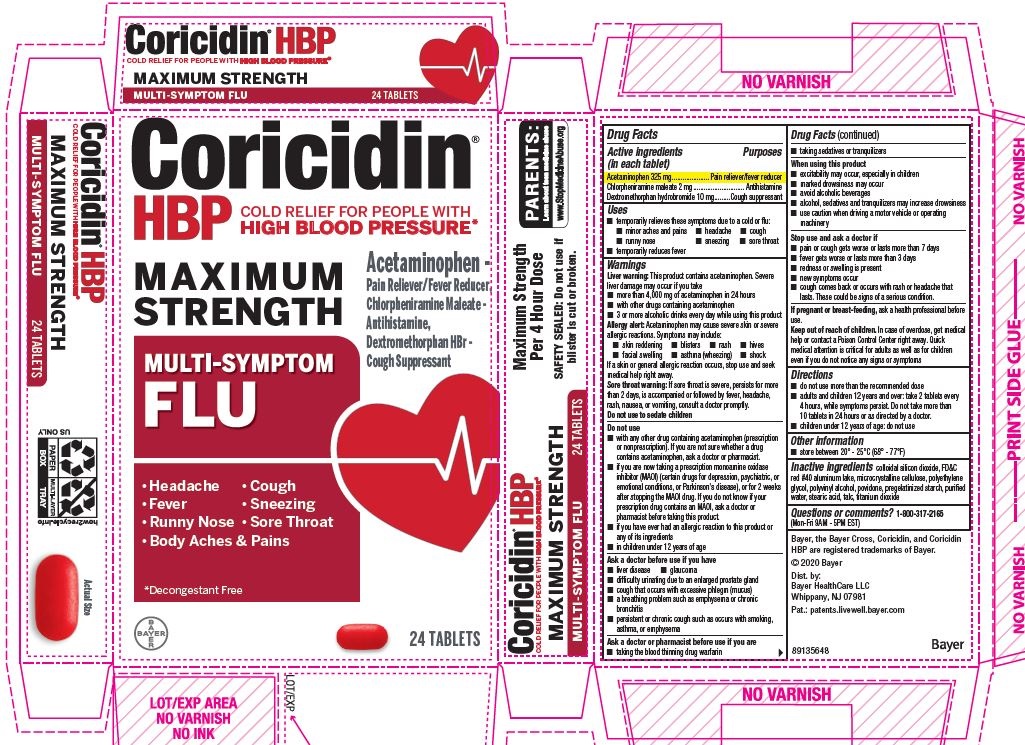 DRUG LABEL: Coricidin HBP Maximum Strength Multi Symptom Flu
NDC: 11523-0038 | Form: TABLET
Manufacturer: Bayer HealthCare LLC.
Category: otc | Type: HUMAN OTC DRUG LABEL
Date: 20251204

ACTIVE INGREDIENTS: DEXTROMETHORPHAN HYDROBROMIDE 10 mg/1 1; ACETAMINOPHEN 325 mg/1 1; CHLORPHENIRAMINE MALEATE 2 mg/1 1
INACTIVE INGREDIENTS: TALC; STARCH, CORN; MICROCRYSTALLINE CELLULOSE; TITANIUM DIOXIDE; POLYETHYLENE GLYCOL, UNSPECIFIED; FD&C RED NO. 40; POVIDONE; STEARIC ACID

Coricidin HBP Max Strength Multi-symptom Flu (tablet) new product name Perrigo Old name Coricidin HBP Max Strength (tablet)

Coricidin HBP

Maximum Strength Multi-Symptom Flu

Drug Facts

Active Ingredient

Active ingredients (in each tablet) Purposes

Acetaminophen 325 mg………………….………….Pain reliever/fever reducer

Chlorpheniramine maleate 2 mg……….......................................Antihistamine

Dextromethorphan hydrobromide 10 mg…………………..Cough suppressant

Uses

- temporarily relieves these symptoms due to a cold or flu:
- minor aches and pains
- headache
- cough
- runny nose
- sneezing
- sore throat
- temporarily reduces fever

Warnings

Liver warning

Liver warning: This product contains acetaminophen. Severe liver damage may occur if you take

- more than 4,000 mg of acetaminophen in 24 hours
- with other drugs containing acetaminophen
- 3 or more alcoholic drinks every day while using this product

Allergy Alert

Allergy alert: Acetaminophen may cause severe skin or severe

allergic reactions. Symptoms may include:

- skin reddening
- blisters
- rash
- hives
- facial swelling
- asthma (wheezing)
- shock

If a skin or general allergic reaction occurs, stop use and seek medical help right away.

Sore throat warning: If sore throat is severe, persists for more than 2 days, is accompanied or followed by fever, headache, rash, nausea, or vomiting, consult a doctor promptly.

Do not use

- with any other drug containing acetaminophen (prescription or nonprescription). If you are not sure whether a drug contains acetaminophen, ask a doctor or pharmacist.
- if you are now taking a prescription monoamine oxidase inhibitor (MAOI) (certain drugs for depression, psychiatric, or emotional conditions, or Parkinson's disease), or for 2 weeks after stopping the MAOI drug. If you do not know if your prescription drug contains an MAOI, ask a doctor or pharmacist before taking this product.
- if you have ever had an allergic reaction to this product or any of its ingredients

Ask a doctor before use if you have

- liver disease
- trouble urinating due to an enlarged prostate gland
- cough that occurs with excessive phlegm (mucus)
- a breathing problem or persistent or chronic cough as occurs with smoking, asthma, chronic bronchitis, or emphysema

When using this product

- excitability may occur, especially in children
- marked drowsiness may occur
- avoid alcoholic beverages
- alcohol, sedatives and tranquilizers may increase drowsiness
- use caution when driving a motor vehicle or operating machinery

Ask a doctor or pharmacist before use if you are

- taking the blood thinning drug warfarin
- taking sedatives or tranquilizers

Stop use and ask a doctor if

- pain or cough gets worse or lasts more than 7 days
- fever gets worse or lasts more than 3 days
- redness or swelling is present
- new symptoms occur
- cough comes back or occurs with rash or headache that lasts. These could be signs of a serious condition.

PREGNANCY OR BREAST FEEDING

If pregnant or breast-feeding, ask a health professional before use.

Keep out of reach of children. Abuse of this product can lead to serious injury.

Overdose warning

Overdose warning: Taking more than the recommended dose may cause liver damage. In case of overdose, get medical help or contact a Poison Control Center right away. Quick medical attention is critical for adults as well as children even if you do not notice any signs or symptoms.

Directions

do not use more than directed (see overdose warning)

adults and children 12 years and over: take 2 tablets every 4 hours, while symptoms persist. Do not take more than 10 tablets in 24 hours or as directed by a doctor.

children under 12 years of age: ask a doctor

Other information

store at room temperature. Avoid excessive heat.

INACTIVE INGREDIENT

Inactive ingredients FD&C red #40 aluminum lake, lecithin, microcrystalline cellulose, polyethylene glycol, polyvinyl alcohol, povidone, pregelatinized starch, stearic acid, talc, titanium dioxide

Questions or comments? 1-800-317-2165 (Mon-Fri 9AM - 5PM EST)

Carton

Coricidin®

HBP COLD RELIEF FOR PEOPLE WITH

HIGH BLOOD PRESSUREƗ

MAXIMUM STRENGTH

MULTI-SYMPTOM

FLU

Relieves

- Body Aches & Pains
- Headache
- Fever
- Cough
- Runny Nose & Sneezing
- Sore Throat

ƗDecongestant Free

24 tablets

Acetaminophen - Pain Reliever/Fever Reducer

Chlorpheniramine Maleate - Antihistamine

Dextromethorphan HBr - Cough Supressant

LEARN MORE

American Heart Association

Information Enclosed